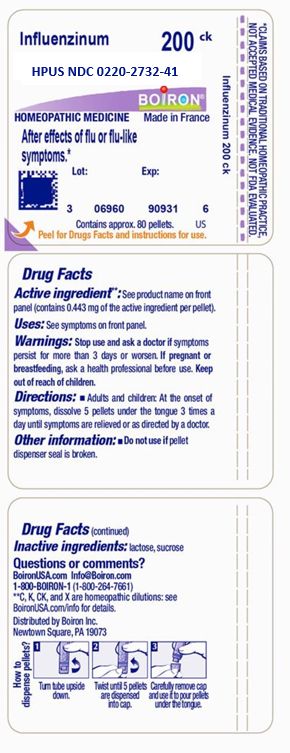 DRUG LABEL: INFLUENZINUM
NDC: 0220-2732 | Form: PELLET
Manufacturer: Boiron
Category: homeopathic | Type: HUMAN OTC DRUG LABEL
Date: 20230720

ACTIVE INGREDIENTS: INFLUENZA A VIRUS A/DARWIN/9/2021 IVR-228 (H3N2) HEMAGGLUTININ ANTIGEN (UV, FORMALDEHYDE INACTIVATED) 200 [kp_C]/200 [kp_C]; INFLUENZA A VIRUS A/VICTORIA/2570/2019 IVR-215 (H1N1) HEMAGGLUTININ ANTIGEN (FORMALDEHYDE INACTIVATED) 200 [kp_C]/200 [kp_C]; INFLUENZA B VIRUS B/MICHIGAN/01/2021 HEMAGGLUTININ ANTIGEN (FORMALDEHYDE INACTIVATED) 200 [kp_C]/200 [kp_C]; INFLUENZA B VIRUS B/PHUKET/3073/2013 HEMAGGLUTININ ANTIGEN (FORMALDEHYDE INACTIVATED) 200 [kp_C]/200 [kp_C]
INACTIVE INGREDIENTS: SUCROSE; LACTOSE, UNSPECIFIED FORM

INFLUENZINUM 200CK MD

ACTIVE INGREDIENT

INFLUENZINUM 200CK HPUS**

(** contains 0.443 mg of the active ingredient per pellet)

INFLUENZA A VIRUS A/VICTORIA/2570/2019 IVR-215 (H1N1) HEMAGGLUTININ ANTIGEN (FORMALDEHYDE INACTIVATED)

INFLUENZA A VIRUS A/DARWIN/9/2021 IVR-228 (H3N2) HEMAGGLUTININ ANTIGEN (UV, FORMALDEHYDE INACTIVATED)

INFLUENZA B VIRUS B/MICHIGAN/01/2021 HEMAGGLUTININ ANTIGEN (FORMALDEHYDE INACTIVATED)

INFLUENZA B VIRUS B/PHUKET/3073/2013 HEMAGGLUTININ ANTIGEN (FORMALDEHYDE INACTIVATED)

INDICATIONS AND USAGE

After effects of flu or flu-like symptoms*

Stop use and ask a doctor if symptoms persist for more than 3 days or worsen.

PREGNANCY OR BREAST FEEDING

If pregnant or breastfeeding, ask a health professional before use.

Keep out of reach of children.

DOSAGE AND ADMINISTRATION

Adults and children: At the onset of symptoms, dissolve 5 pellets under the tongue 3 times a day until symptoms are relieved or as directed by a doctor.

Do not use if pellet dispenser seal is broken.
Contains approx. 80 pellets.
How to dispense pellets? Turn tube upside down. Twist until 5 pellets are dispensed into cap. Carefully remove the cap and use it to pour pellets under the tongue.
*CLAIMS BASED ON TRADITIONAL HOMEOPATHIC PRACTICE NOT ACCEPTED MEDICAL EVIDENCE. NOT FDA EVALUATED.
*C,K,CK, and X are homeopathic dilutions: see BoironUSA.com/info for details.

INACTIVE INGREDIENT

lactose, sucrose

QUESTIONS

Made in France

1-800-BOIRON-1 (1-800-264-7661),
BoironUSA.com Info@boiron.com
Distributed by Boiron, Inc. Newtown Square, PA 19073